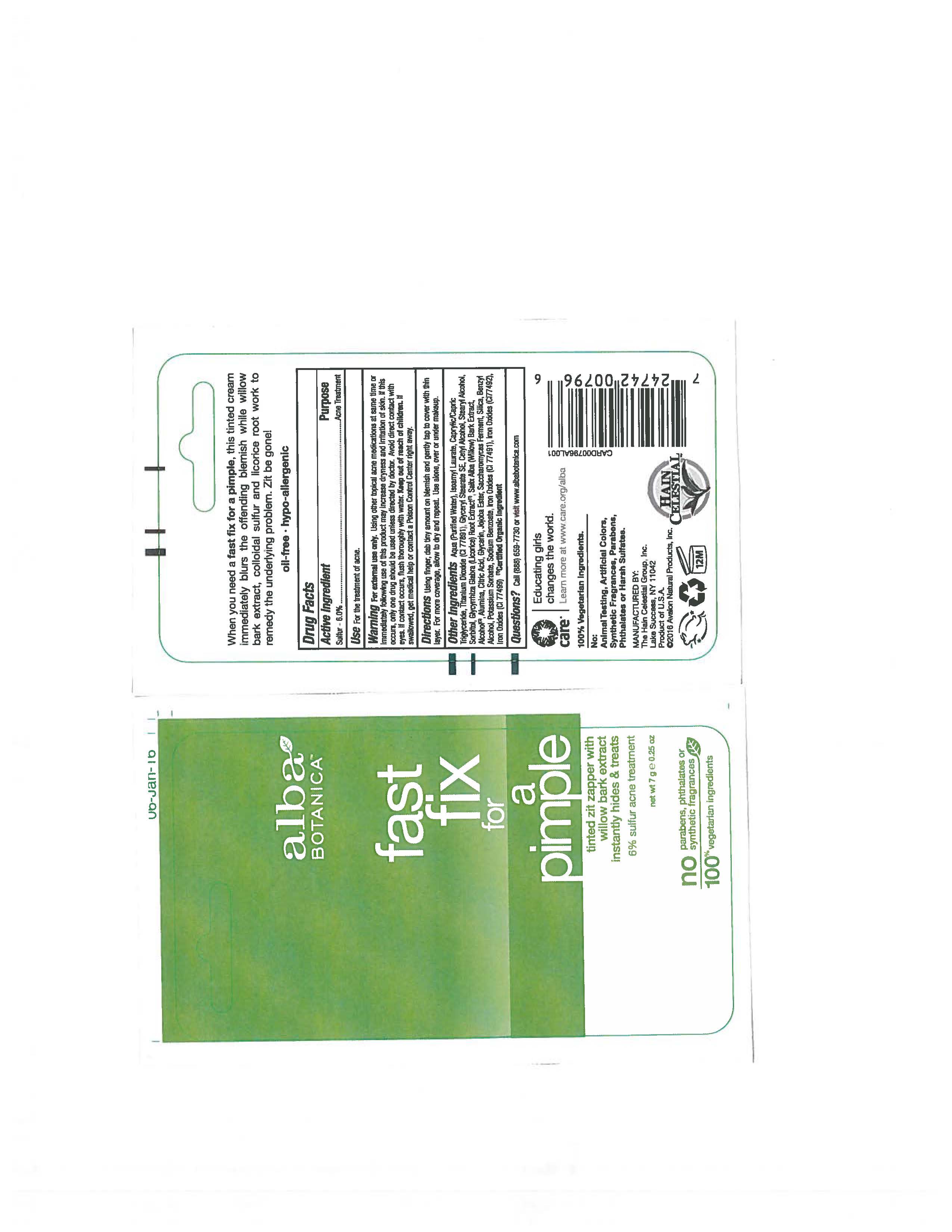 DRUG LABEL: Alba Botanica Fast Fix for Pimple
NDC: 61995-2796 | Form: CREAM
Manufacturer: The Hain Celestial Group, Inc.
Category: otc | Type: HUMAN OTC DRUG LABEL
Date: 20210205

ACTIVE INGREDIENTS: SULFUR 6 g/100 g
INACTIVE INGREDIENTS: SILICON DIOXIDE; POTASSIUM SORBATE; GLYCYRRHIZA GLABRA; SALIX ALBA BARK; WATER; GLYCERIN; MEDIUM-CHAIN TRIGLYCERIDES; CETOSTEARYL ALCOHOL; ANHYDROUS CITRIC ACID; SODIUM BENZOATE; SACCHAROMYCES LYSATE; BROWN IRON OXIDE; ISOAMYL LAURATE; SORBITOL; ALCOHOL; ALUMINUM OXIDE; JOJOBA OIL, RANDOMIZED; BENZYL ALCOHOL; TITANIUM DIOXIDE; GLYCERYL STEARATE SE; CETYL ALCOHOL

Alba Botanica Fast Fix for Pimples

Active Ingredient

Sulfur 6.0%

DOSAGE AND ADMINISTRATION

Using finger, dab tiny amount on blemishand gently tap to cover with thin layer. For more coverage allow to dry and repeat. Use alone, over or under makeup.

PURPOSE

Acne Treatment

WARNINGS

For external use only. Using other topical acne medications at the same time or immediately following the use of this product may increase dryness and irritation of the skin. If this occurs, only one drug should be used unless directed by a doctor. Avoid direct contact with eyes. If contact occurs, flush throughly with water.

Keep out of reach of children. If swallowed get medical help or contact Poison Center right away.

INACTIVE INGREDIENT

Water, Isoamyl Laurate, Caprylic/Capric Triglyceride, Titanium Dioxide (CI77891), Glyceryl Stearate SE, Glycyrrhiza Glabra (Licorice) Root Extract, Salix Alba (Willow) Bark Extract (1), Alcohol (1), Alumina, Stearyl Alcohol, Cetyl Alcohol, Citric Acid, Glycerin, Jojoba Ester, Saccharomyces Ferment, Silica, Benzyl Alcohol, Potassium Sorbate, Sodium Benzoate, Iron Oxides (CI77491).

(1) Certified Organicf Ingredient;

INDICATIONS AND USAGE

For the treatment of acne.